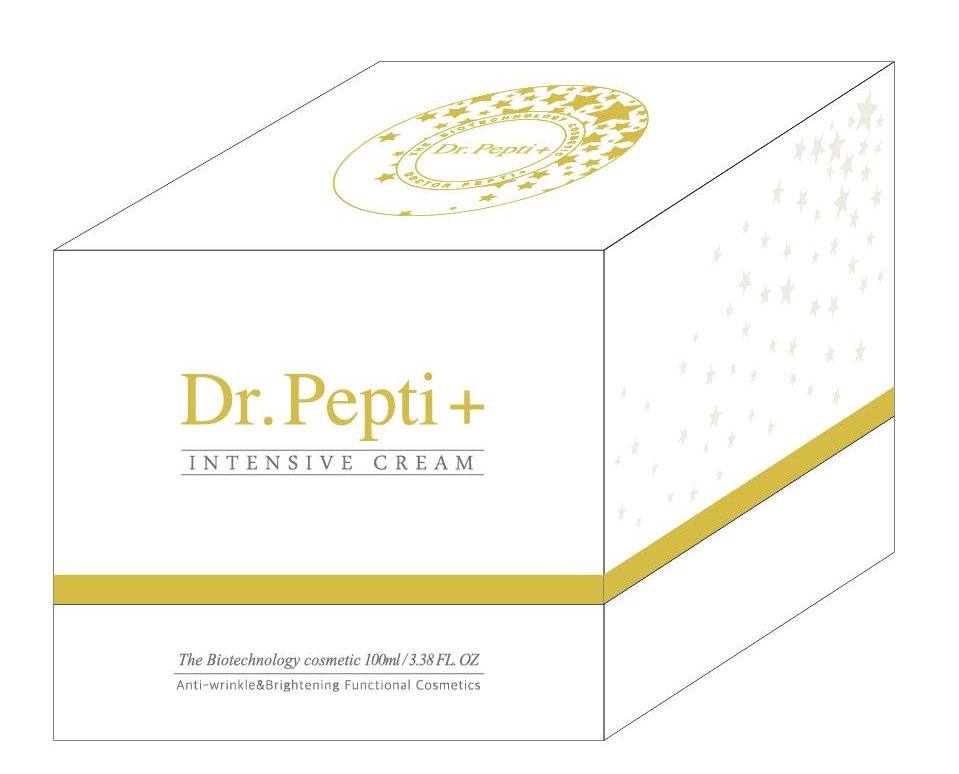 DRUG LABEL: Dr. Pepti INTENSIVE
NDC: 71146-0002 | Form: CREAM
Manufacturer: J&COCEU Co Ltd
Category: otc | Type: HUMAN OTC DRUG LABEL
Date: 20161221

ACTIVE INGREDIENTS: NIACINAMIDE 2 g/100 mL; ADENOSINE 0.04 g/100 mL
INACTIVE INGREDIENTS: WATER; BUTYLENE GLYCOL; GLYCERIN

Drug Facts

ACTIVE INGREDIENT

Niacinamide, Adenosine

INACTIVE INGREDIENT

Glycerin, Water, Butylene Glycol, Betaine, Allantoin, Sodium Hyaluronate, etc.

PURPOSE

whitening
anti wrinkle

INDICATIONS AND USAGE

Apply after toner, paint appropriate amount on the skin. Please absorbs Pat it lightly in skin.

keep out of reach of the children

WARNINGS

For external use only. Avoid contact with eyes and mouth.

Discontinue use if signs of irritation or rash appear.

Keep out of reach of children. Replace the cap after use.

DOSAGE AND ADMINISTRATION

for external use only